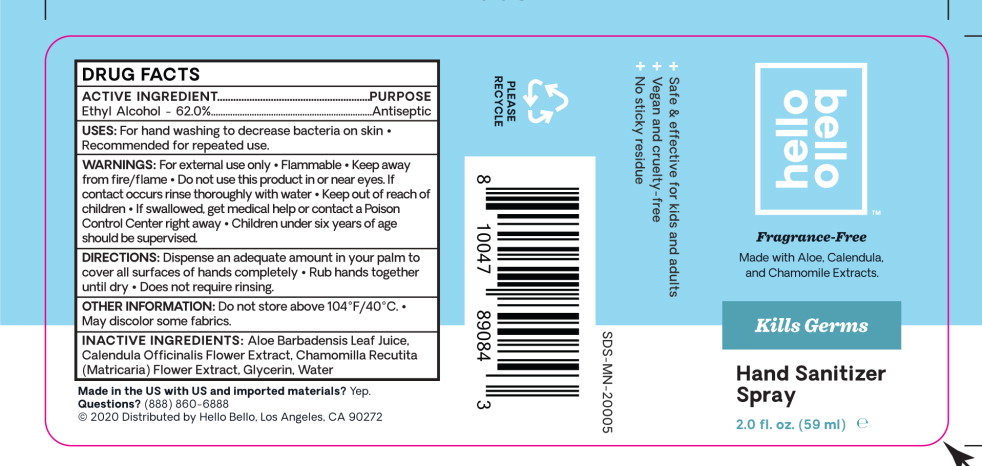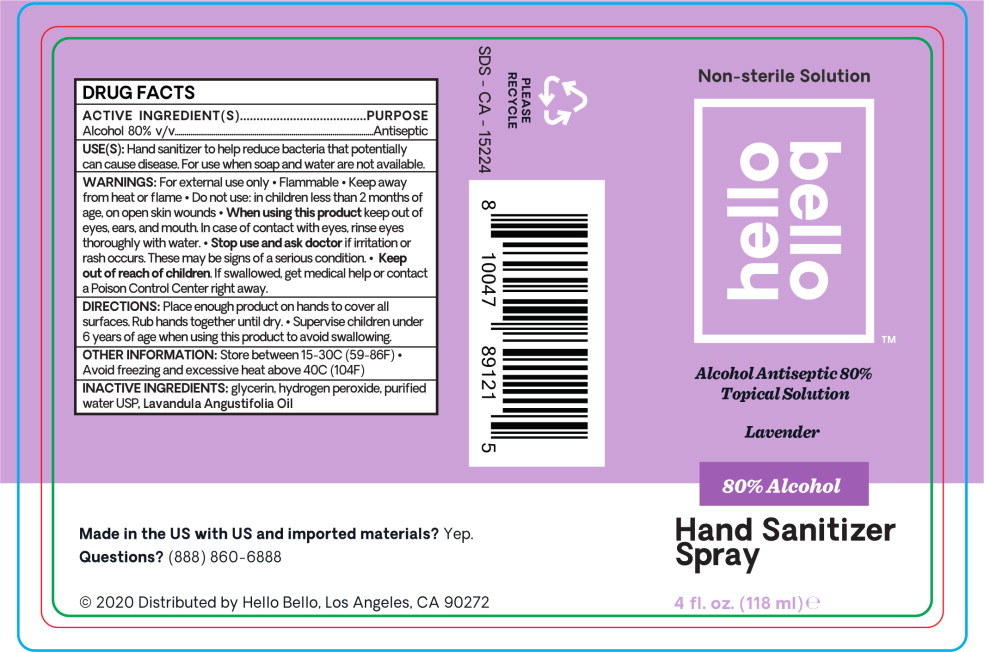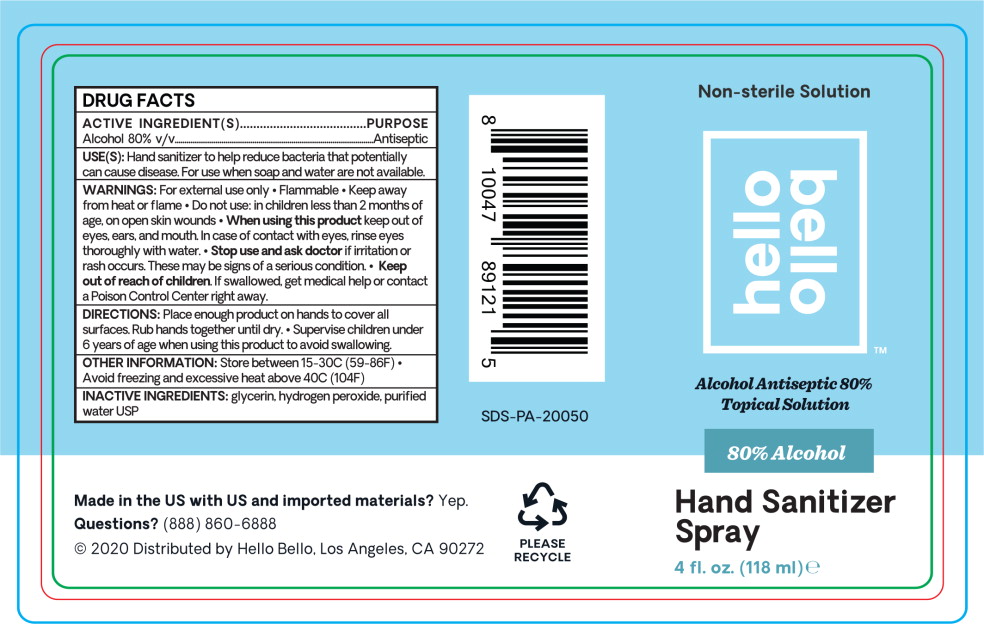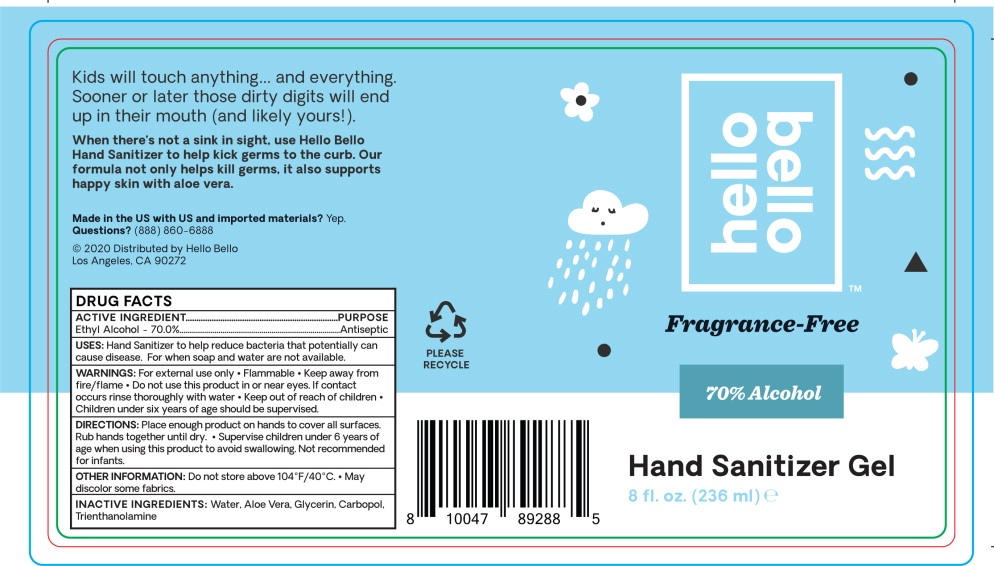 DRUG LABEL: Alcohol
NDC: 73418-030 | Form: LIQUID
Manufacturer: Hello Bello
Category: otc | Type: HUMAN OTC DRUG LABEL
Date: 20210209

ACTIVE INGREDIENTS: Alcohol 62 mL/100 mL
INACTIVE INGREDIENTS: Aloe Vera Leaf; Calendula Officinalis Flower; Chamomile; Glycerin; Water

DRUG FACTS

ACTIVE INGREDIENT

Ethyl Alcohol - 62.0%

PURPOSE

Antiseptic

USES:

For hand washing to decrease bacteria on skin

- Recommended for repeated use.

WARNINGS:

For external use only

- Flammable
- Keep away from fire/flame

- Do not use this product in or near eyes. If contact occurs rinse thoroughly with water

- Keep out of reach of children
- If swallowed, get medical help or contact a Poison Control Center right away
- Children under six years of age should be supervised.

DIRECTIONS:

Dispense an adequate amount in your palm to cover all surfaces of hands completely

- Rub hands together until dry
- Does not require rinsing.

OTHER INFORMATION:

Do not store above 104°F/40°C.

- May discolor some fabrics.

INACTIVE INGREDIENTS:

Aloe Barbadensis Leaf Juice. Calendula Officinalis Flower Extract Chamomilla Recutita (Matricaria) Flower Extract, Glycerin, Water

Principal Display Panel – 59 mL Bottle Label

hello
bello™

Fragrance-Free

Made with Aloe, Calendula,
and Chamomile Extracts.

+ Safe & effective for kids and adults
+ Vegan and cruelty-free
+ No sticky residue

Kills Germs

Hand Sanitizer
Spray

2.0 fl. oz. (59 ml) e

Principal Display Panel – 118 mL Bottle Label

Non-Sterile Solution

hello
bello™

Alcohol Antiseptic 80%
Topical Solution

Lavender

80% Alcohol

Hand Sanitizer
Spray

4 fl. oz. (118 ml) e

Principal Display Panel – 118 mL Bottle Label

Non-Sterile Solution

hello
bello™

Alcohol Antiseptic 80%
Topical Solution

80% Alcohol

Hand Sanitizer
Spray

4 fl. oz. (118 ml) e

Principal Display Panel – 236 mL Bottle Label

hello
bello™

Fragrance-Free

70% Alcohol

Hand Sanitizer Gel

8 fl. oz. (236 ml) e